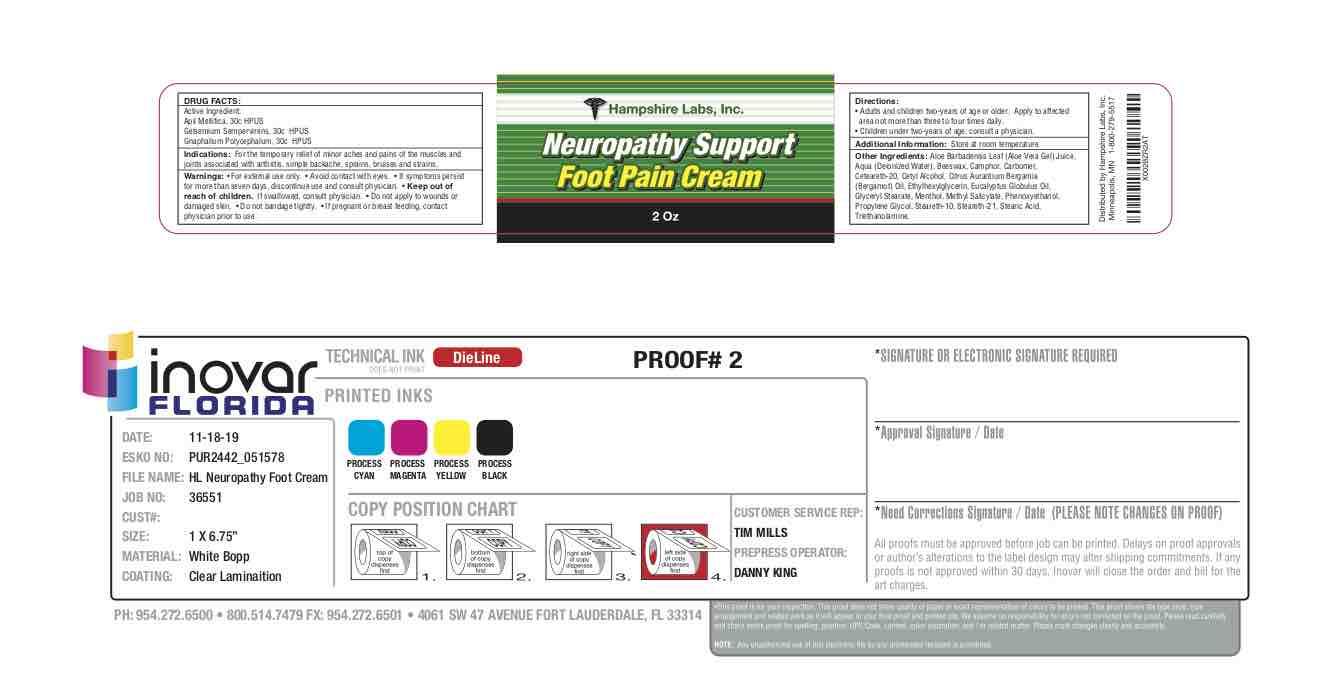 DRUG LABEL: Neuropathy Support Foot Pain Cream
NDC: 71423-001 | Form: CREAM
Manufacturer: Hampshire Labs, LLC
Category: homeopathic | Type: HUMAN OTC DRUG LABEL
Date: 20191119

ACTIVE INGREDIENTS: APIS MELLIFERA 30 [hp_C]/1 mL; GELSEMIUM SEMPERVIRENS ROOT 30 [hp_C]/1 mL; PSEUDOGNAPHALIUM OBTUSIFOLIUM 30 [hp_C]/1 mL
INACTIVE INGREDIENTS: MENTHOL; STEARIC ACID; TROLAMINE; CAMPHOR (NATURAL); YELLOW WAX; POLYOXYL 20 CETOSTEARYL ETHER; CETYL ALCOHOL; ALOE VERA LEAF; CARBOMER 940; ETHYLHEXYLGLYCERIN; METHYL SALICYLATE; PHENOXYETHANOL; PROPYLENE GLYCOL; STEARETH-10; EUCALYPTUS GLOBULUS LEAF; GLYCERYL STEARATE CITRATE; STEARETH-21; CITRUS BERGAMIA LEAF OIL

Neuropathy Support Foot Pain Cream

Active Ingredient:

Apil Mellifica, 30c HPUS

Gelsemium Sempervirens, 30c HPUS

Gnaphalium Polycephalum, 30c HPUS

INDICATIONS AND USAGE

Indications: For the temporary relief of minor aches and pains of the muscles and

joints associated with arthritis, simple backache, sprains, bruises and strains.

WARNINGS

Warnings: • For external use only. • Avoid contact with eyes.

ASK DOCTOR

If symptoms persist for more than seven days, discontinue use and consult physician.

Keep out of reach of children. If swallowed, consult physician.

WHEN USING

Do not apply to wounds or damaged skin. • Do not bandage tightly

PREGNANCY OR BREAST FEEDING

If pregnant or breast feeding, contact physician prior to use.

DIRECTIONS

• Adults and children two-years of age or older: Apply to affected area not more than three to four times daily. • Children under two-years of age: consult a physician.

ADDITIONAL INFORMATION

Store at room temperature.

INACTIVE INGREDIENT

Aloe Barbadensis Leaf (Aloe Vera Gel) Juice,

Aqua (Deionized Water), Beeswax, Camphor, Carbomer,

Ceteareth-20, Cetyl Alcohol, Citrus Aurantium Bergamia

(Bergamot) Oil, Ethylhexylglycerin, Eucalyptus Globulus Oil,

Glyceryl Stearate, Menthol, Methyl Salicylate, Phenoxyethanol,

Propylene Glycol, Steareth-10, Steareth-21, Stearic Acid,

Triethanolamine.

PURPOSE

Homeopathic Foot Cream for Pain Relief